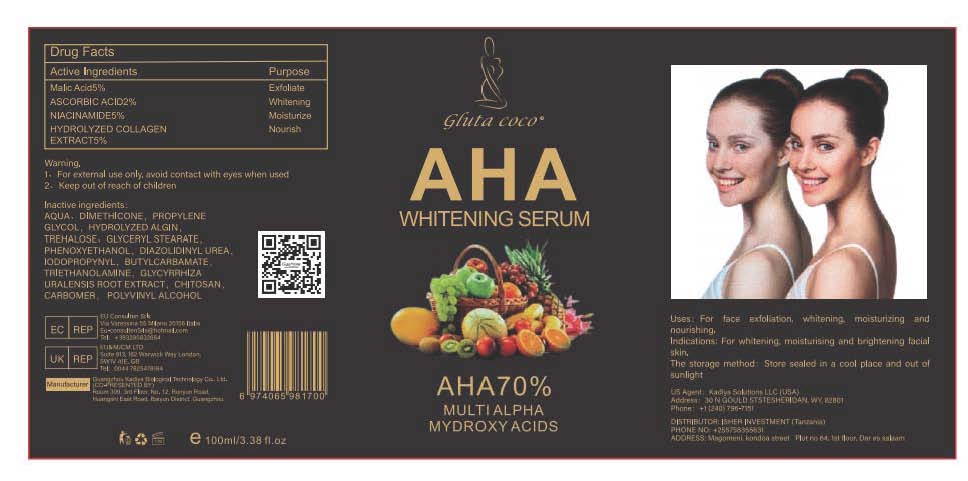 DRUG LABEL: IAHA WHITENING SERUM
NDC: 84423-070 | Form: CREAM, AUGMENTED
Manufacturer: Guangzhou Kadiya Biotechnology Co., Ltd.
Category: otc | Type: HUMAN OTC DRUG LABEL
Date: 20250217

ACTIVE INGREDIENTS: NIACINAMIDE 5 g/100 mL; MALIC ACID 5 g/100 mL; ASCORBIC ACID 2 g/100 mL
INACTIVE INGREDIENTS: PHENOXYETHANOL; POLYVINYL ALCOHOL; DIMETHICONE; GLYCYRRHIZA URALENSIS ROOT; POLIGLUSAM; CARBOMER; AQUA; PROPYLENE GLYCOL; LAMINARIA DIGITATA HYDROLYZED ALGINIC ACID; TREHALOSE; GLYCERYL STEARATE; TROLAMINE; IODOPROPYNYL BUTYLCARBAMATE; DIAZOLIDINYL UREA

PURPOSE

For face exfoliation, whitening, moisturizing and nourishing.

INACTIVE INGREDIENT

AQUA、DIMETHICONE，PROPYLENE GLYCOL，HYDROLYZED ALGIN，TREHALOSE、GLYCERYL STEARATE，PHENOXYETHANOL，DIAZOLIDINYL UREA，IODOPROPYNYL，BUTYLCARBAMATE，TRIETHANOLAMINE，GLYCYRRHIZA URALENSIS ROOT EXTRACT，CHITOSAN，CARBOMER， POLYVINYL ALCOHOL

Warning.
1、For external use only, avoid contact with eyes when used
2、Keep out of reach of children

INDICATIONS AND USAGE

For whitening, moisturising and brightening facialskin.

DOSAGE AND ADMINISTRATION

For face exfoliation, whitening, moisturizing and nourishing.

KEEP OUT OF REACH OF CHILDREN SECTION

Active Ingredients
Malic Acid5%
ASCORBIC ACID2%
NIACINAMIDE5%
HYDROLYZED COLLAGEN EXTRACT5%

PACKAGE LABEL

Active Ingredients
Malic Acid5%
ASCORBIC ACID2%
NIACINAMIDE5%
HYDROLYZED COLLAGEN EXTRACT5%

Uses：
For face exfoliation, whitening, moisturizing and nourishing.
Indications: For whitening, moisturising and brightening facial skin.
The storage method：
Store sealed in a cool place and out of sunlight

Warning.
1、For external use only, avoid contact with eyes when used
2、Keep out of reach of children

Inactive ingredients：
AQUA、DIMETHICONE，PROPYLENE GLYCOL，HYDROLYZED ALGIN，TREHALOSE、GLYCERYL STEARATE，PHENOXYETHANOL，DIAZOLIDINYL UREA，IODOPROPYNYL，BUTYLCARBAMATE，TRIETHANOLAMINE，GLYCYRRHIZA URALENSIS ROOT EXTRACT，CHITOSAN，CARBOMER， POLYVINYL ALCOHOL